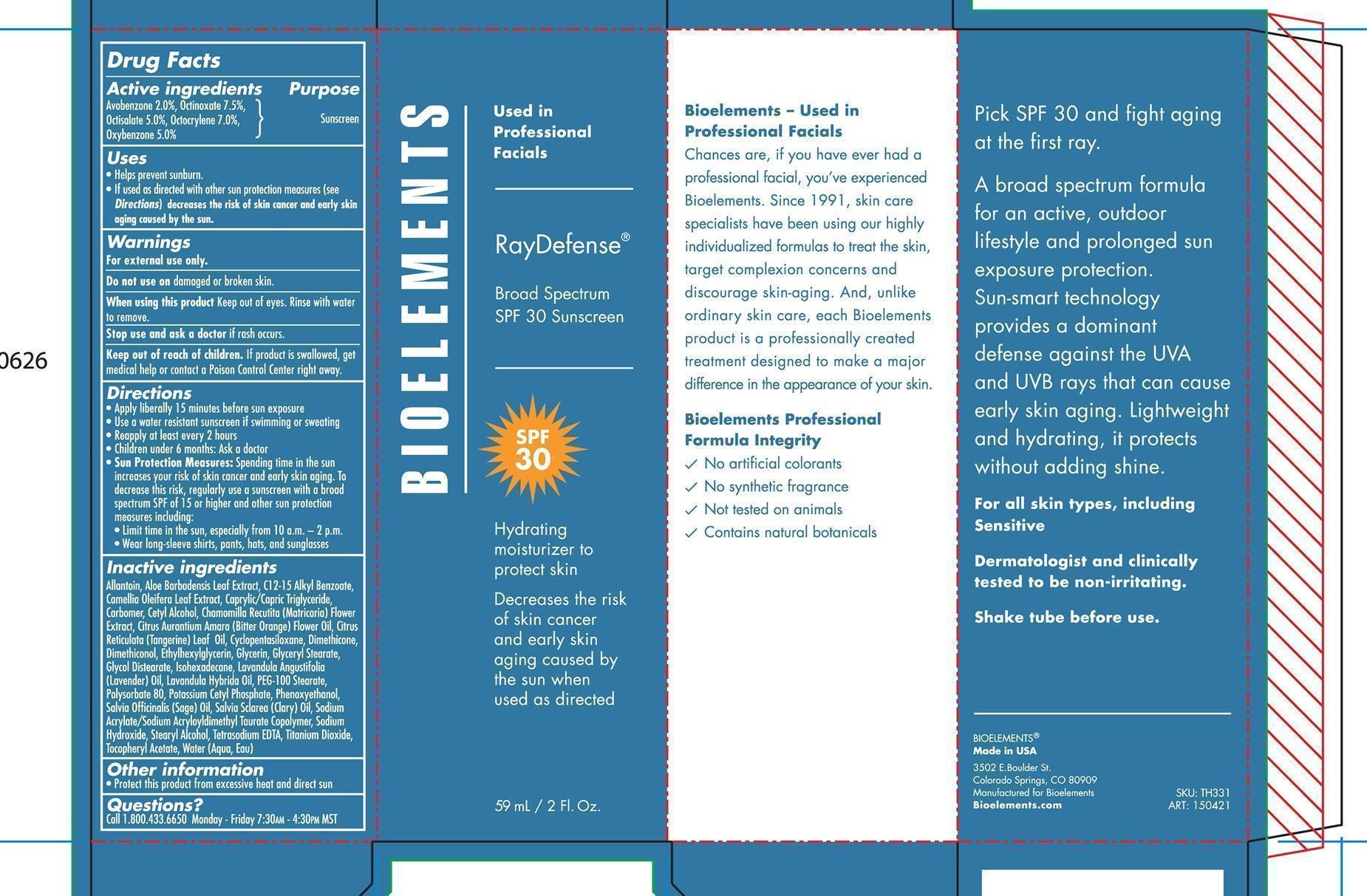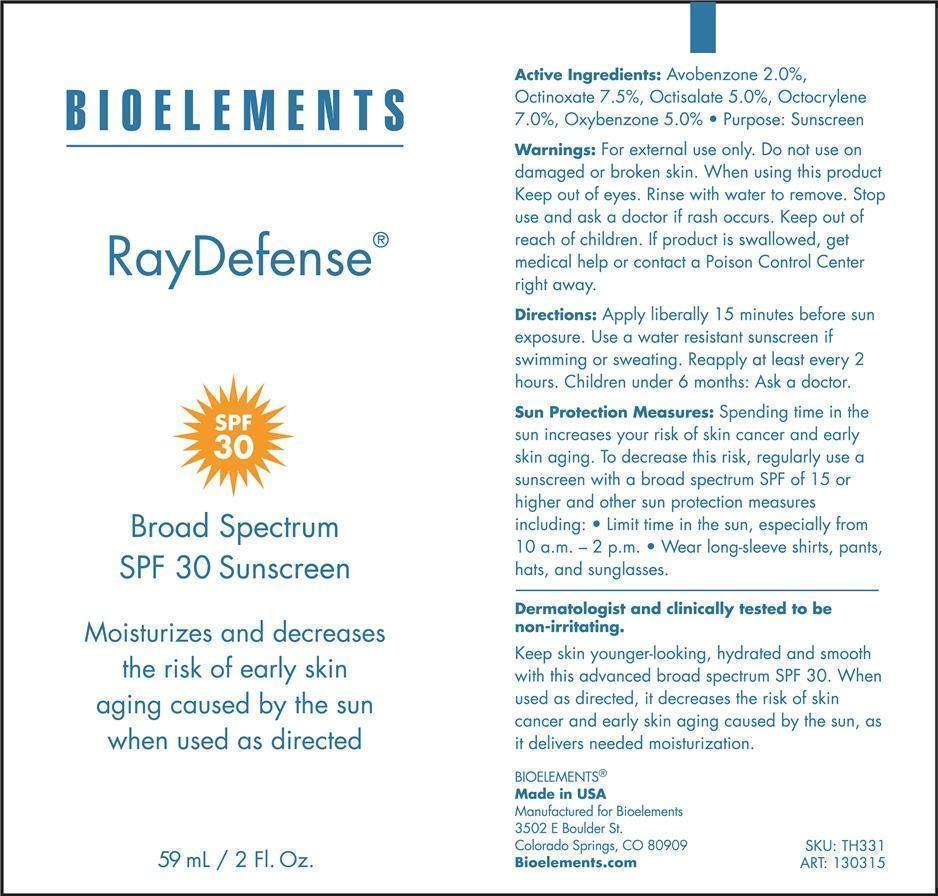 DRUG LABEL: Ray Defense
NDC: 49825-138 | Form: CREAM
Manufacturer: Bioelements
Category: otc | Type: HUMAN OTC DRUG LABEL
Date: 20251217

ACTIVE INGREDIENTS: AVOBENZONE 2 g/100 mL; OCTINOXATE 7.5 g/100 mL; OCTISALATE 5 g/100 mL; OCTOCRYLENE 7 g/100 mL; OXYBENZONE 5 g/100 mL
INACTIVE INGREDIENTS: ALLANTOIN; ALOE VERA LEAF; ALKYL (C12-15) BENZOATE; CAMELLIA OLEIFERA LEAF; MEDIUM-CHAIN TRIGLYCERIDES; CARBOMER 940; CETYL ALCOHOL; CHAMOMILE; CITRUS AURANTIUM FLOWER OIL; CITRUS RETICULATA LEAF OIL; CYCLOMETHICONE 5; DIMETHICONE; ETHYLHEXYLGLYCERIN; GLYCERIN; GLYCERYL STEARATE SE; GLYCOL DISTEARATE; ISOHEXADECANE; LAVENDER OIL; LAVANDIN OIL; PEG-100 STEARATE; POLYSORBATE 80; POTASSIUM CETYL PHOSPHATE; PHENOXYETHANOL; SAGE OIL; CLARY SAGE OIL; SODIUM ACRYLATE/SODIUM ACRYLOYLDIMETHYLTAURATE COPOLYMER (4000000 MW); SODIUM HYDROXIDE; STEARYL ALCOHOL; EDETATE SODIUM; TITANIUM DIOXIDE; .ALPHA.-TOCOPHEROL ACETATE; WATER

Ray Defense - Broad Spectrum SPF 30 Sunscreen

Active Ingredients Purpose

Avobenzone 2.0% ......... Sunscreen

Octinoxate 7.5% ........... Sunscreen

Octisalate 5.0% ............ Sunscreen

Octocrylene 7.0% ......... Sunscreen

Oxybenzone 5.0% ........ Sunscreen

PURPOSE

- Helps prevent sunburn
- If used as directed with other sun protection measures (see Directions) decreases the risk of skin cancer and early skin aging caused by the sun

Keep out of reach of children.If product is swallowed, get medical help or contact a Poison Control Center right away

Stop use and ask a doctorif rash occurs

WARNINGS

- For external use only

- Do not use on damaged or broken skin

- When using this productkeep out of eyes. Rinse with water to remove.

DOSAGE AND ADMINISTRATION

- Apply liberally 15 minutes before sun exposure
- Use a water resistan sunscreen if swimming or sweating
- Reapply at least every 2 hours
- Children under 6 months: Ask a doctor
- Sun Protection Measures:Spending time in the sun increases your risk of skin cancer and early skin aging. To decrease this risk, regularly use a sunscreen with a broad spectrum SPF of 15 or higher and other sun protection measures including:
- Limit time in the sun, especially from 10 a.m - 2 p.m.
- Wear long-sleeve shirts, pants, hats, and sunglasses

Inactive Ingredients

Allantoin, Aloe Barbadensis Leaf Extract, C12-15 Alkyl Benzoate, Camellia Oleifera Leaf Extract, Caprylic/Capric Triglyceride, Carbomer, Cetyl Alcoho, Cahmomilla Recutita (Matricaria) Flower Extract, Citrus Aurantium Amara (Bitter Orange) Flower Oil, Citrus Reticulata (Tangerine) Leaf Oil, Cyclopentasiloxane Dimethicone, Dimethiconol, Ethylhexylglycerin, Glycerin, Glyceryl Stearate, Glycol Distearate, Isohexadecane, Lavandula Angustifolia (Lavender) Oil, Lavandula Hybrida Oil, PEG-100 Stearate, Polysorbate 80, Potassium Cetyl Phosphate, Phenoxyethanol, Salvia Officinalis (Sage) Oil, Salvia Sclarea (Clary) Oil, Sodium Acrylate/Sodium Acryloyldimethyl Taurate Copolymer, Sodium Hydroxide, Stearyl Alcohol, Tetrasodium EDTA, Titanium Dioxide, Tocopheryl Acetate, Water (Aqua, Eau)

PACKAGE LABEL

Ray Defense

Broad Spectrum

SPF 30 Sunscreen

59 mL. / 2 Fl. OZ